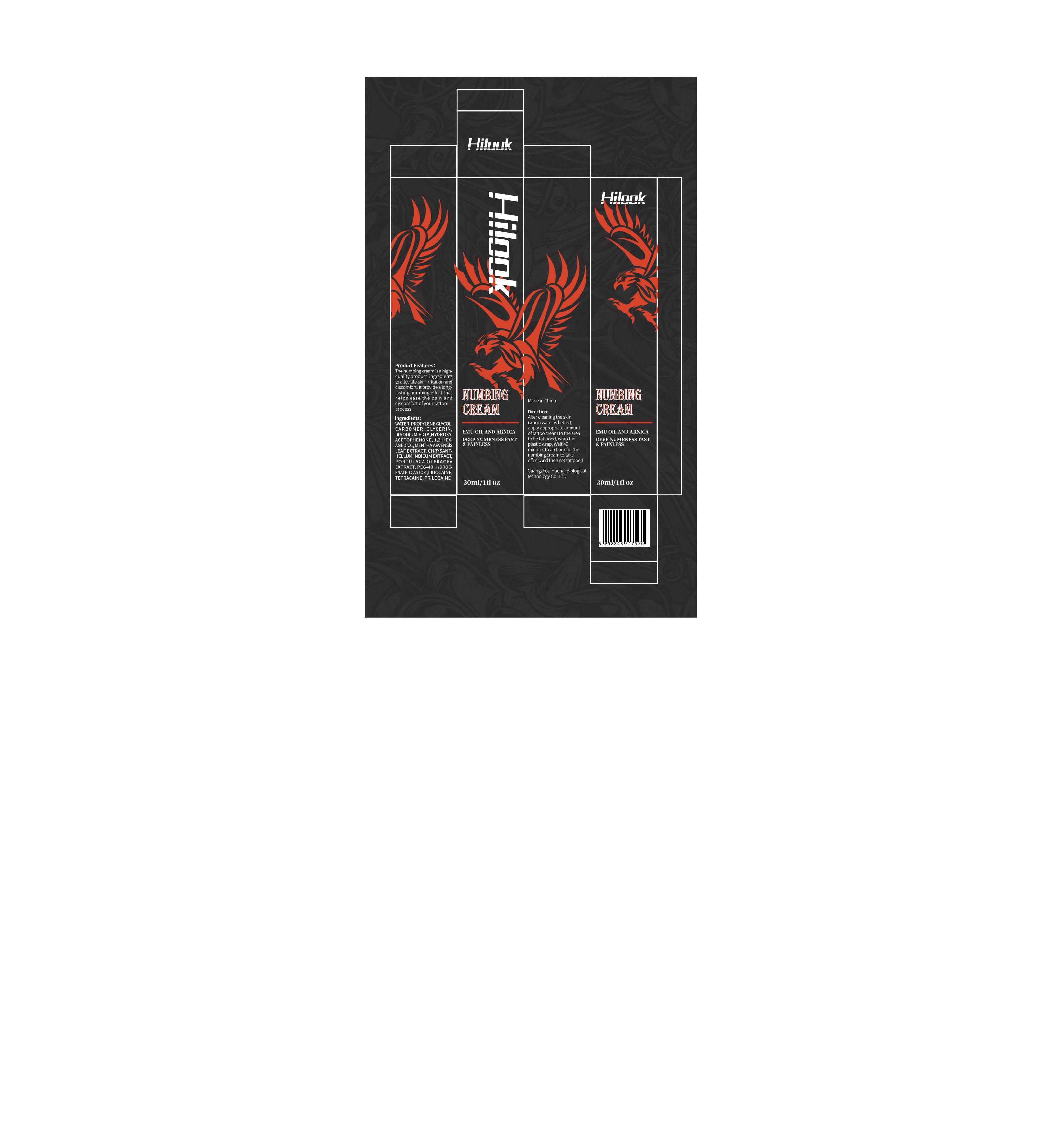 DRUG LABEL: Hilook Numbing Cream
NDC: 83566-142 | Form: CREAM
Manufacturer: Guangdong Aimu Biological Technology Co., Ltd
Category: otc | Type: HUMAN OTC DRUG LABEL
Date: 20250625

ACTIVE INGREDIENTS: TETRACAINE 1 g/100 mL; PRILOCAINE 1 g/100 mL; LIDOCAINE 5 g/100 mL
INACTIVE INGREDIENTS: GLYCERIN; PEG-40 HYDROGENATED LANOLIN; 1,2-HEXANEDIOL

Hilook Numbing Cream

Active ingredients

LIDOCAINE 5%
TETRACAINE 1%
PRILOCAINE 1%

Purpose

Deep numbness fast and painless

Uses

After cleaning the skin(warm water is better), apply appropriate amount of tattoo cream to the area to be tattooed, wrap the plastic wrap,.

Wait 40 minutes to an hour for the numbing cream to take effect.

And then get tattooed.

Warnings

For external use only.

Stop use and ask a doctor if

rash occurs.

Do not use

on damaged or broken skin.

When using this product

keep out of eyes. Rinse with water to remove.

Keep out of reach of children.

If swallowed, get medical help or contact a Poison Control Center right away.

Dosage

Squeeze out an appropriate amount of product and spread evenly on skin.

Inactive ingredients

WATER 51.8%
PROPYLENE GLYCOL 10%
CARBOMER 3%
GLYCERIN 15%
DISODIUM EDTA 0.2%
HYDROXYACETOPHENONE 1.5%
1,2-HEXANEDIOL 1.5%
MENTHAARVENSIS LEAF EXTRACT 2%
CHRYSANTHELLUM INDICUM EXTRACT 2%
PORTULACA OLERACEA EXTRACT 3%
PEG-40 HYDROGENATED CASTOR 3